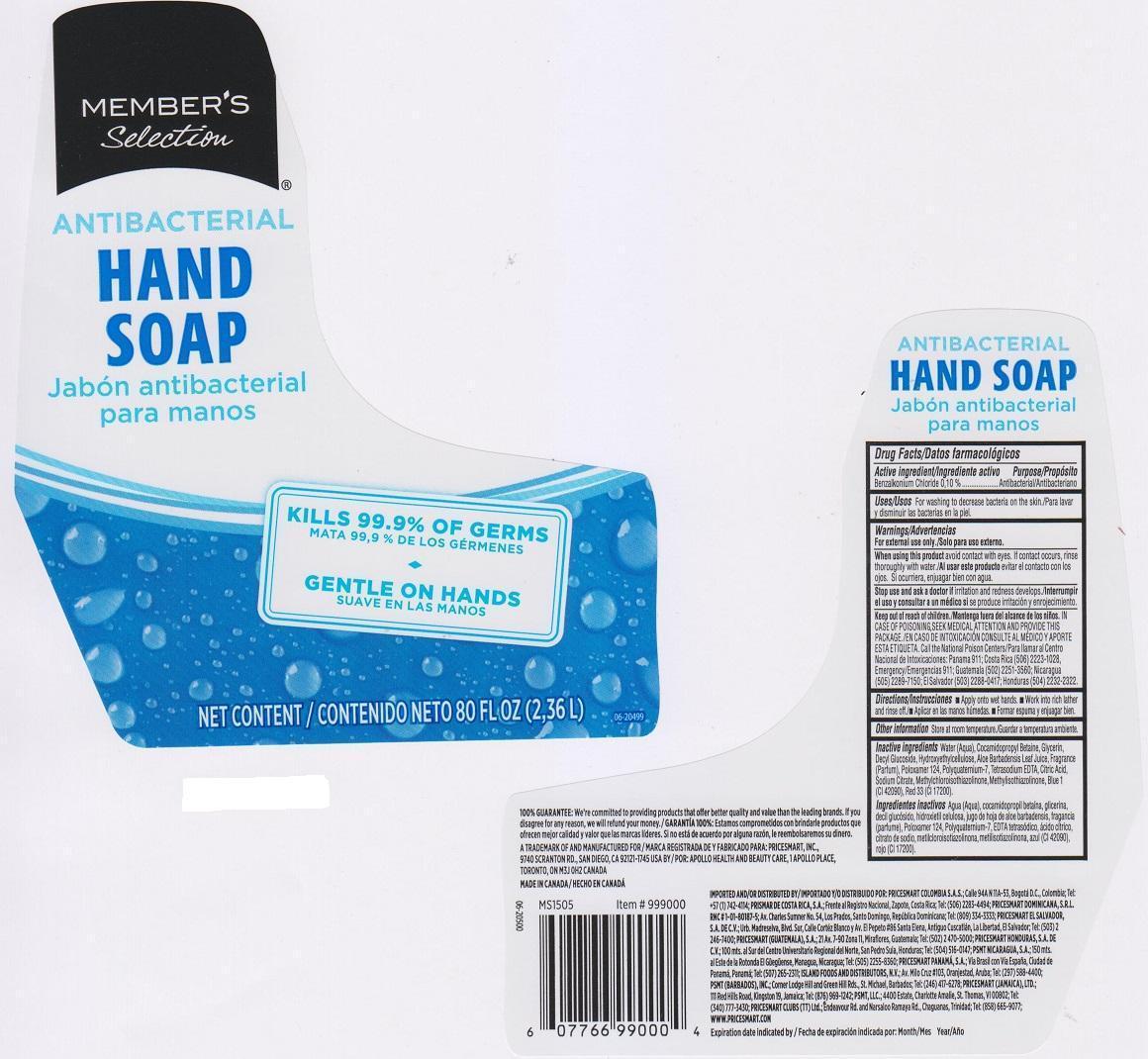 DRUG LABEL: MEMBERS SELECTION ANTIBACTERIAL
NDC: 63148-079 | Form: LIQUID
Manufacturer: APOLLO HEALTH AND BEAUTY CARE
Category: otc | Type: HUMAN OTC DRUG LABEL
Date: 20150810

ACTIVE INGREDIENTS: BENZALKONIUM CHLORIDE 1 mg/1 mL
INACTIVE INGREDIENTS: WATER; COCAMIDOPROPYL BETAINE; GLYCERIN; DECYL GLUCOSIDE; HYPROMELLOSES; ALOE VERA LEAF; POLOXAMER 124; POLYQUATERNIUM-7 (70/30 ACRYLAMIDE/DADMAC; 1600000 MW); EDETATE SODIUM; CITRIC ACID MONOHYDRATE; SODIUM CITRATE; METHYLCHLOROISOTHIAZOLINONE; METHYLISOTHIAZOLINONE; FD&C BLUE NO. 1; D&C RED NO. 33

Active ingredient / Ingrediente activo

Benzalkonium Chloride 0.10%

Purpose / Propósito

Antibacterial / Antibacteriano

Uses / Usos

For washing to decrease bacteria on the skin. / Para lavar y disminuir las bacterias en la piel

Warnings / Advertencias

For external use only / Solo para uso externo

When using this product / Al usar este producto

avoid contact with eyes. If contact occurs, rinse thoroughly with water. / evitar el contacto con los ojos. Si ocurriera, enjuagar bien con agua.

Stop use and ask a doctor if / Interrumpir el uso y consultar a un médico si

irritation and redness develops. / se product irritación y enrojecimiento

Keep out of reach of children. / Mantenga fuera del alcance de los niños.

In case of poisoning, seek medical attention and provide this package. Call the National Poison Centers / En caso de intoxicación consulte al médico y aporte esta etiqueta. Para llamar al Centro Nacional de Intoxicaciones: Panama 911; Costa Rica (506) 2223-1028, Emergency/Emergencias 911; Guatemala (502) 2251-3560; Nicaragua (505) 2289-7150; El Salvador (503) 2288-0417; Honduras (504) 2232-2322

Directions / Instrucciones

- Apply onto wet hands / Aplicar en las manos húmedas
- Work into rich later and rinse off / Formar espuma y enjuagar bien

Other Information

Store at room temperature / Guardar a temperatura ambiente

Inactive ingredients / Ingredientes inactivos

Water (Aqua), Cocamidopropyl Betaine, Glycerin, Decyl Glucosid, Hydroxyethylcellulose, Aloe Barbadensis Leaf Juice, Fragrance (Parfum), Poloxamer 124, Polyquaternium-7, Tetrasodium EDTA, Citric Acid, Sodium Citrate, Methylchloroisothiazolinone, Methylisothiazolinone, Blue 1 (CI 42090), Red 33 (CI 17200).

Agua (Aqua), Cocamidopropil betaína, glicerina, decil glucósido, hidroxietil celulosa, jugo de hoja de aloe barbadensis, fragrancia (parfume), poloxamer 124, policuaternio 7, EDTA tetrasódico, ácido cítrico, citrato de sodio, meticloroisotiazolinona, metilisotiasolinona, azul (CI 42090), rojo (CI 17200)